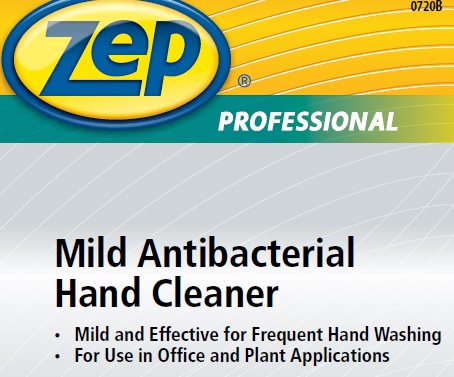 DRUG LABEL: Zep Professional Mild AB
NDC: 66949-130 | Form: LIQUID
Manufacturer: Zep Inc.
Category: otc | Type: HUMAN OTC DRUG LABEL
Date: 20251226

ACTIVE INGREDIENTS: BENZALKONIUM CHLORIDE 0.13 g/100 mL
INACTIVE INGREDIENTS: LAUROYL/MYRISTOYL AMIDOPROPYL AMINE OXIDE; GLYCERIN; ANHYDROUS CITRIC ACID; METHYLCHLOROISOTHIAZOLINONE; EDETATE SODIUM; FD&C RED NO. 4; CETRIMONIUM CHLORIDE; COCO DIISOPROPANOLAMIDE; FD&C YELLOW NO. 5; SODIUM CHLORIDE; WATER; PEG-120 METHYL GLUCOSE DIOLEATE; METHYLISOTHIAZOLINONE

66949-130 / R399 Zep Professional Mild AB

Active Ingredient

Benzalkonium Chloride 0.13%

Purpose

Antiseptic Handwash

Uses

Hand washing to decrease bacteria on skin.

Warnings

For external use only.

Do not use in the eyes; if in eyes, rinse promptly and thoroughly with water.

When using this product

- Do not swallow.
- If swallowed, do not induce vomiting and if individual is conscious, give large quantities of water to drink and consult a physician immediately.

Stop use and ask a doctor if skin irritation or redness persists for more than 72 hours.

Keep out of reach of children except under adult supervision.

Directions

- Wet hands with water.
- Place hands under dispenser and apply liquid soap.
- Massage soap into hands and wrists, emphasizing back of hands, knuckles, and cuticles.
- Rinse hands thoroughly and dry.

Other Information

- Store at room temperature.
- Do not freeze.
- Dispose in accordance with all applicable federal, state, and local regulations.

Inactive ingredients

Water, Cetrimonium Chloride, Lauryl/Myristyl Amidopropyl Amine Oxide, Glycerin, Cocamide DIPA, PEG-120 Methyl Glucose Dioleate, Sodium Chloride, Citric Acid, Methylchloroisothiazolinone, Methylisothiazolinone, Tetrasodium EDTA, Fragrance, Yellow 5, Red 4

Questions or comments?

Call 1-877-BUY-ZEP (1-877-428-9937)